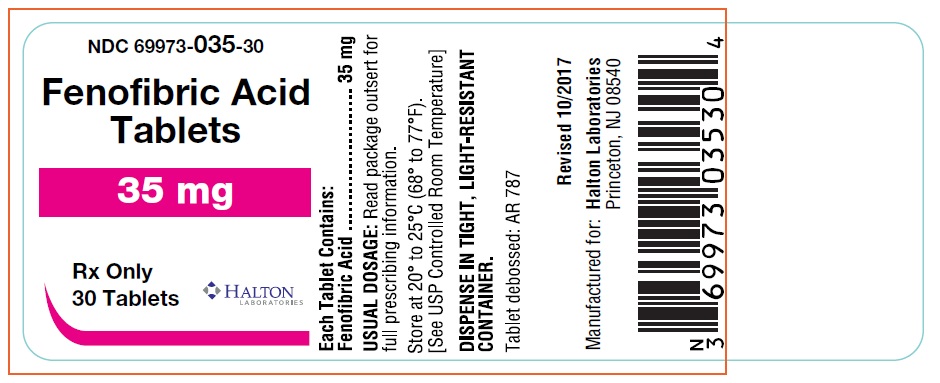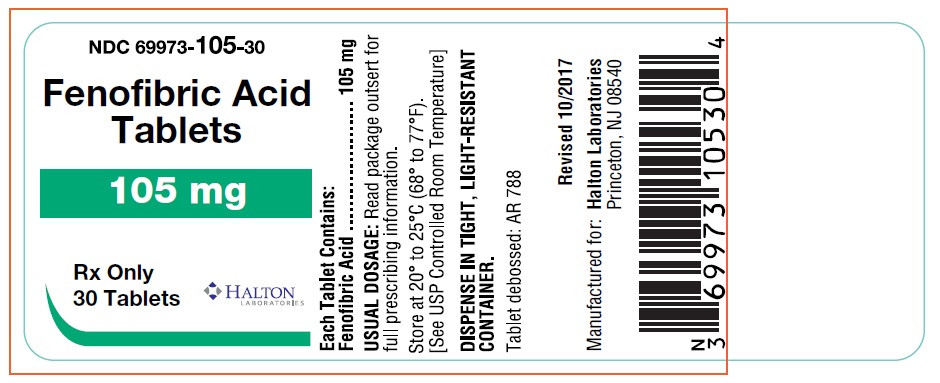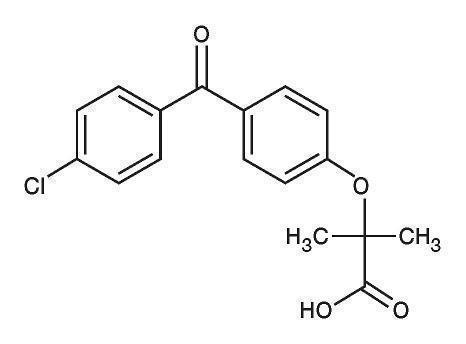 DRUG LABEL: Fenofibric Acid
NDC: 69973-035 | Form: TABLET
Manufacturer: Halton Laboratories
Category: prescription | Type: HUMAN PRESCRIPTION DRUG LABEL
Date: 20181010

ACTIVE INGREDIENTS: Fenofibric Acid 35 mg/1 1
INACTIVE INGREDIENTS: Copovidone K25-31; crospovidone; magnesium stearate; cellulose, microcrystalline

HIGHLIGHTS OF PRESCRIBING INFORMATION

These highlights do not include all the information needed to use fenofibric acid tablets safely and effectively. See full prescribing information for fenofibric acid tablets.
Fenofibric Acid Tablets, for oral use
Initial U.S. Approval: 1993

1 INDICATIONS AND USAGE

Fenofibric acid tablets are a peroxisome proliferator receptor alpha (PPARα) activator indicated as an adjunct to diet:

- to reduce triglyceride (TG) levels in adult patients with severe hypertriglyceridemia (≥ 500 mg/dL) (1.1).
- to reduce elevated total cholesterol (TC), low-density-lipoprotein cholesterol (LDL-C), TG and apolipoprotein (Apo) B and to increase high-density lipoprotein cholesterol (HDL-C) in adult patients with primary hypercholesterolemia or mixed dyslipidemia (1.2).

Important Limitations of Use: Fenofibrate was not shown to reduce coronary heart disease morbidity and mortality in patients with type 2 diabetes mellitus (1.3).

2 DOSAGE AND ADMINISTRATION

- Fenofibric acid tablets may be taken without regards to meals (2.1).
- Severe hypertriglyceridemia: 35 to 105 mg/day; the dose should be adjusted according to patient response (2.2).
- Primary hypercholesterolemia or mixed dyslipidemia: 105 mg/day (2.3).
- Renally impaired patients: Initial dose of 35 mg once daily (2.4).
- Geriatric patients: Select the dose on the basis of renal function (2.5).

3 DOSAGE FORMS AND STRENGTHS

Oral Tablets: 35 mg and 105 mg (3)

4 CONTRAINDICATIONS

- Severe renal dysfunction, including patients receiving dialysis (4)
- Active liver disease (4)
- Gallbladder disease (4)
- Nursing Mothers (4)
- Known hypersensitivity to fenofibric acid or fenofibrate (4)

5 WARNINGS AND PRECAUTIONS

- Myopathy and rhabdomyolysis have been reported in patients taking fenofibrate. The risks of myopathy and rhabdomyolysis appears to be increased when fibrates are co-administered with a statin (with a significantly higher rate observed for gemfibrozil), particularly in elderly patients and patients with diabetes, renal failure, or hypothyroidism (5.2).
- Fenofibrate can increase serum transaminases. Monitor liver tests, including ALT, periodically during therapy (5.3).
- Fenofibrate can reversibly increase serum creatinine levels. Monitor renal function periodically in patients with renal insufficiency (5.4).
- Fenofibrate increases cholesterol excretion into the bile, leading to risk of cholelithiasis. If cholelithiasis is suspected, gallbladder studies are indicated (5.5).
- Exercise caution in concomitant treatment with oral coumarin anticoagulants. Adjust the dosage of coumarin anticoagulant to maintain the prothrombin time/INR at the desired level to prevent bleeding complications (5.6).
- Acute hypersensitivity reactions, including anaphylaxis and angioedema, and delayed hypersensitivity reactions, including severe cutaneous adverse drug reactions have been reported postmarketing. Some cases, were life-threatening and required emergency treatment. Discontinue fenofibrate and treat patients appropriately if reactions occur (5.9).

6 ADVERSE REACTIONS

Most common adverse reactions (> 2% and at least 1% greater than placebo) are abnormal liver tests, increased AST, increased ALT, increased CPK, and rhinitis (6).
To report SUSPECTED ADVERSE REACTIONS, contact Halton Laboratories at 1-866-391-4503 or FDA at 1-800-FDA-1088 or www.fda.gov/medwatch.

7 DRUG INTERACTIONS

- Coumarin Anticoagulants (7.1)
- Bile-Acid Binding Resins (7.2)
- Immunosuppressants (7.3)
- Colchicine (7.4)

8 USE IN SPECIFIC POPULATIONS

- Geriatric Use: Determine dose selection based on renal function (8.5).
- Renal Impairment: Avoid in patients with severe renal impairment; dose reduction required in patients with mild-to-moderate renal impairment (8.6).

RECENT MAJOR CHANGES

Warnings and Precautions (5.9) – 05/2018

FULL PRESCRIBING INFORMATION

1 INDICATIONS AND USAGE

1.1 Severe Hypertriglyceridemia

Fenofibric acid tablets are indicated as adjunctive therapy to diet for treatment of severe hypertriglyceridemia (≥ 500 mg/dL). Improving glycemic control in diabetic patients showing fasting chylomicronemia will usually obviate the need for pharmacologic intervention.

Markedly elevated levels of serum triglycerides > 2000 mg/dL may increase the risk of developing pancreatitis. The effect of fenofibrate therapy on reducing this risk has not been adequately studied.

1.2 Primary Hypercholesterolemia or Mixed Dyslipidemia

Fenofibric acid tablets are indicated as adjunctive therapy to diet to reduce elevated low-density lipoprotein cholesterol (LDL-C), total cholesterol (Total-C), triglycerides (TG), and apolipoprotein B (Apo B), and to increase high-density lipoprotein cholesterol (HDL-C) in patients with primary hypercholesterolemia or mixed dyslipidemia.

1.3 Important Limitations of Use

Fenofibrate at a dose equivalent to 105 mg of fenofibric acid tablets was not shown to reduce coronary heart disease morbidity and mortality in patients with type 2 diabetes mellitus [see Warnings and Precautions (5.1)].

2 DOSAGE AND ADMINISTRATION

2.1 General Considerations

Fenofibric acid tablets can be given without regard to meals. Patients should be advised to swallow fenofibric acid tablets whole. Do not crush, dissolve or chew tablets.

Patients should be placed on an appropriate lipid-lowering diet before receiving fenofibric acid tablets and should continue this diet during treatment with fenofibric acid.

The initial treatment for dyslipidemia is dietary therapy specific for the type of lipoprotein abnormality. Excess body weight and excess alcoholic intake may be important factors in hypertriglyceridemia and should be addressed prior to any drug therapy. Physical exercise can be an important ancillary measure. Diseases contributory to hyperlipidemia, such as hypothyroidism or diabetes mellitus should be looked for and adequately treated. Estrogen therapy, thiazide diuretics and beta-blockers, are sometimes associated with massive rises in plasma triglycerides, especially in subjects with familial hypertriglyceridemia. In such cases, discontinuation of the specific etiologic agent may obviate the need for specific drug therapy of hypertriglyceridemia.

Periodic determination of serum lipids should be obtained during initial therapy in order to establish the lowest effective dose of fenofibric acid tablets. Therapy should be withdrawn in patients who do not have an adequate response after two months of treatment with the maximum recommended dose of 105 mg per day.

Consideration should be given to reducing the dosage of fenofibric acid tablets if lipid levels fall significantly below the targeted range.

2.2 Severe Hypertriglyceridemia

The initial dose is 35 to 105 mg per day. Dosage should be individualized according to patient response, and should be adjusted if necessary following repeat lipid determinations at 4 to 8 week intervals. The maximum dose is 105 mg once daily.

2.3 Primary Hypercholesterolemia or Mixed Dyslipidemia

The dose of fenofibric acid tablets is 105 mg per day.

2.4 Impaired Renal Function

In patients with mild-to-moderate renal impairment, treatment with fenofibric acid tablets should be initiated at a dose of 35 mg once daily, and increased only after evaluation of the effects on renal function and lipid levels at this dose. The use of fenofibric acid tablets should be avoided in patients with severe renal impairment [see Use in Specific Populations (8.6) and Clinical Pharmacology (12.3)].

2.5 Geriatric Patients

Dose selection for the elderly should be made on the basis of renal function [see Use in Specific Populations (8.5) and Clinical Pharmacology (12.3)].

3 DOSAGE FORMS AND STRENGTHS

- 35-mg: White, round tablets. Debossed "AR 787".
- 105-mg: White, modified oval tablets. Debossed "AR 788".

4 CONTRAINDICATIONS

Fenofibric acid tablets are contraindicated in:

- patients with severe renal impairment, including those receiving dialysis [see Clinical Pharmacology (12.3)].
- patients with active liver disease, including those with primary biliary cirrhosis and unexplained persistent liver function abnormalities [see Warnings and Precautions (5.3)].
- patients with preexisting gallbladder disease [see Warnings and Precautions (5.5)].
- patients with known hypersensitivity to fenofibric acid or fenofibrate [see Warnings and Precautions (5.9)].
- nursing mothers [see Use in Specific Populations (8.3)].

5 WARNINGS AND PRECAUTIONS

5.1 Mortality and Coronary Heart Disease Morbidity

The effect of fenofibric acid tablets on coronary heart disease morbidity and mortality and non-cardiovascular mortality has not been established.

The Action to Control Cardiovascular Risk in Diabetes Lipid (ACCORD Lipid) trial was a randomized placebo-controlled study of 5518 patients with type 2 diabetes mellitus on background statin therapy treated with fenofibrate. The mean duration of follow-up was 4.7 years. Fenofibrate plus statin combination therapy showed a non-significant 8% relative risk reduction in the primary outcome of major adverse cardiovascular events (MACE), a composite of non-fatal myocardial infarction, non-fatal stroke, and cardiovascular disease death (hazard ratio [HR] 0.92, 95% CI 0.79–1.08) (p=0.32) as compared to statin monotherapy. In a gender subgroup analysis, the hazard ratio for MACE in men receiving combination therapy versus statin monotherapy was 0.82 (95% CI 0.69–0.99), and the hazard ratio for MACE in women receiving combination therapy versus statin monotherapy was 1.38 (95% CI 0.98–1.94) (interaction p=0.01). The clinical significance of this subgroup finding is unclear.

The Fenofibrate Intervention and Event Lowering in Diabetes (FIELD) study was a 5 year randomized, placebo-controlled study of 9795 patients with type 2 diabetes mellitus treated with fenofibrate. Fenofibrate demonstrated a non-significant 11% relative reduction in the primary outcome of coronary heart disease events (hazard ratio [HR] 0.89, 95% CI 0.75–1.05, p=0.16) and a significant 11% reduction in the secondary outcome of total cardiovascular disease events (HR 0.89 [0.80–0.99], p=0.04). There was a non-significant 11% (HR 1.11 [0.95, 1.29], p=0.18) and 19% (HR 1.19 [0.90, 1.57], p=0.22) increase in total and coronary heart disease mortality, respectively, with fenofibrate as compared to placebo.

Because of chemical, pharmacological, and clinical similarities between fenofibrate, clofibrate, and gemfibrozil, the adverse findings in 4 large randomized, placebo-controlled clinical studies with these other fibrate drugs may also apply to fenofibric acid.

In the Coronary Drug Project, a large study of post myocardial infarction of patients treated for 5 years with clofibrate, there was no difference in mortality seen between the clofibrate group and the placebo group. There was however, a difference in the rate of cholelithiasis and cholecystitis requiring surgery between the two groups (3.0% vs. 1.8%).

In a study conducted by the World Health Organization (WHO), 5000 subjects without known coronary artery disease were treated with placebo or clofibrate for 5 years and followed for an additional one year. There was a statistically significant, higher age – adjusted all-cause mortality in the clofibrate group compared with the placebo group (5.70% vs. 3.96%, p<0.01). Excess mortality was due to a 33% increase in non-cardiovascular causes, including malignancy, post-cholecystectomy complications, and pancreatitis. This appeared to confirm the higher risk of gallbladder disease seen in clofibrate-treated patients studied in the Coronary Drug Project.

The Helsinki Heart Study was a large (n=4081) study of middle-aged men without a history of coronary artery disease. Subjects received either placebo or gemfibrozil for 5 years, with a 3.5 year open extension afterward. Total mortality was numerically higher in the gemfibrozil randomization group but did not achieve statistical significance (p=0.19, 95% confidence interval for relative risk = 0.91–1.64). Although cancer deaths trended higher in the gemfibrozil group (p=0.11), cancers (excluding basal cell carcinoma) were diagnosed with equal frequency in both study groups. Due to the limited size of the study, the relative risk of death from any cause was not shown to be different than that seen in the 9 year follow-up data from World Health Organization study (relative risk=1.29).

A secondary prevention component of the Helsinki Heart Study enrolled middle-aged men excluded from the primary prevention study because of known or suspected coronary heart disease. Subjects received gemfibrozil or placebo for 5 years. Although cardiac deaths trended higher in the gemfibrozil group, this was not statistically significant (HR 2.2, 95% confidence interval: 0.94–5.05).

5.2 Skeletal Muscle

Fibrates increase the risk for myopathy and have been associated with rhabdomyolysis. The risk for serious muscle toxicity appears to be increased in elderly patients and in patients with diabetes, renal failure, or hypothyroidism.

Data from observational studies suggest that the risk for rhabdomyolysis is increased when fibrates, in particular gemfibrozil, are co-administered with an HMG-CoA reductase inhibitor (statin). The combination should be avoided unless the benefit of further alterations in lipid levels is likely to outweigh the increased risk of this drug combination [see Clinical Pharmacology (12.3)].

Myopathy should be considered in any patient with diffuse myalgias, muscle tenderness or weakness, and/or marked elevations of creatine phosphokinase levels.

Patients should be advised to report promptly unexplained muscle pain, tenderness or weakness, particularly if accompanied by malaise or fever. CPK levels should be assessed in patients reporting these symptoms, and fenofibric acid tablets therapy should be discontinued if markedly elevated CPK levels occur or myopathy/myositis is suspected or diagnosed.

Cases of myopathy, including rhabdomyolysis, have been reported with fenofibrates co-administered with colchicine, and caution should be exercised when prescribing fenofibrate with colchicine [see Drug Interactions (7.4)].

5.3 Liver Function

Fenofibrate (administered over a range of doses with the higher dose equivalent to 105 mg fenofibric acid) has been associated with increases in serum transaminases [AST (SGOT) or ALT (SGPT)].

In a pooled analysis of 10 placebo-controlled trials, increases to > 3 times the upper limit of normal of ALT occurred in 5.3% of patients taking fenofibrate versus 1.1% of patients treated with placebo.

When transaminase determinations were followed either after discontinuation of treatment or during continued treatment, a return to normal limits was usually observed. The incidence of increases in transaminases observed with fenofibrate therapy appear to be dose related. In an 8-week dose-ranging study, the incidence of ALT or AST elevations to at least three times the upper limit of normal was 13% in patients receiving dosages equivalent to 35 mg to 105 mg fenofibric acid tablets per day and was 0% in those receiving dosages equivalent to 35 mg or less fenofibric acid tablets per day, or placebo.

Hepatocellular, chronic active and cholestatic hepatitis associated with fenofibrate therapy have been reported after exposures of weeks to several years. In extremely rare cases, cirrhosis has been reported in association with chronic active hepatitis.

Baseline and regular, periodic monitoring of liver function, including ALT (SGPT) should be performed for the duration of therapy with fenofibric acid tablets, and therapy discontinued if enzyme levels persist above three times the normal limit.

5.4 Serum Creatinine

Elevations in serum creatinine have been reported in patients on fenofibrate. These elevations tend to return to baseline following discontinuation of fenofibrate. The clinical significance of these observations is unknown. Renal monitoring should be considered for patients with renal impairment and for patients at risk for renal insufficiency, such as the elderly and patients with diabetes.

5.5 Cholelithiasis

Fenofibric acid tablets, like fenofibrate, clofibrate and gemfibrozil, may increase cholesterol excretion into the bile, leading to cholelithiasis. If cholelithiasis is suspected, gallbladder studies are indicated. Fenofibric acid tablets therapy should be discontinued if gallstones are found.

5.6 Coumarin Anticoagulants

Caution should be exercised when coumarin anticoagulants are given in conjunction with fenofibric acid tablets. Fenofibric acid tablets may potentiate the anticoagulant effects of these agents resulting in prolongation of the prothrombin time/International Normalized Ratio (PT/INR). To prevent bleeding complications, frequent monitoring of PT/INR and dose adjustment of the anticoagulant are recommended until the PT/INR has stabilized [see Drug Interactions (7.1)].

5.7 Pancreatitis

Pancreatitis has been reported in patients taking fenofibrate. This occurrence may represent a failure of efficacy in patients with severe hypertriglyceridemia, a direct drug effect, or a secondary phenomenon mediated through biliary tract stone or sludge formation with obstruction of the common bile duct.

5.8 Hematological Changes

Mild-to-moderate hemoglobin, hematocrit, and white blood cell decreases have been observed in patients following initiation of fenofibrate therapy. However, these levels stabilize during long-term administration. Thrombocytopenia and agranulocytosis have been reported in individuals treated with fenofibrate. Periodic monitoring of red and white blood cell counts is recommended during the first 12 months of fenofibric acid tablets administration.

5.9 Hypersensitivity Reactions

Acute Hypersensitivity

Anaphylaxis and angioedema have been reported postmarketing with fenofibrate. In some cases, reactions were life-threatening and required emergency treatment. If a patient develops signs or symptoms of an acute hypersensitivity reaction, advise them to seek immediate medical attention and discontinue fenofibrate.

Delayed Hypersensitivity

Severe cutaneous adverse drug reactions (SCAR), including Stevens-Johnson Syndrome, Toxic Epidermal Necrolysis, and Drug Reaction with Eosinophilia and Systemic Symptoms (DRESS), have been reported postmarketing, occurring days to weeks after initiation of fenofibrate. The cases of DRESS were associated with cutaneous reactions (such as rash or exfoliative dermatitis) and a combination of eosinophilia, fever, systemic organ involvement (renal, hepatic, or respiratory). Discontinue fenofibrate and treat patients appropriately if SCAR is suspected.

5.10 Venothromboembolic Disease

In the FIELD trial, pulmonary embolus (PE) and deep vein thrombosis (DVT) were observed at higher rates in the fenofibrate- than the placebo-treated group. Of 9,795 patients enrolled in FIELD, there were 4,900 in the placebo group and 4,895 in the fenofibrate group. For DVT, there were 48 events (1%) in the placebo group and 67 (1%) in the fenofibrate group (p=0.074); and for PE, there were 32 (0.7%) events in the placebo group and 53 (1%) in the fenofibrate group (p=0.022).

In the Coronary Drug Project, a higher proportion of the clofibrate group experienced definite or suspected fatal or nonfatal pulmonary embolism or thrombophlebitis than the placebo group (5.2% vs. 3.3% at five years; p<0.01).

5.11 Paradoxical Decreases in HDL Cholesterol Levels

There have been postmarketing and clinical trial reports of severe decreases in HDL cholesterol levels (as low as 2 mg/dL) occurring in diabetic and non-diabetic patients initiated on fibrate therapy. The decrease in HDL-C is mirrored by a decrease in apolipoprotein A1. This decrease has been reported to occur within 2 weeks to years after initiation of fibrate therapy. The HDL-C levels remain depressed until fibrate therapy has been withdrawn; the response to withdrawal of fibrate therapy is rapid and sustained. The clinical significance of this decrease in HDL-C is unknown. It is recommended that HDL-C levels be checked within the first few months after initiation of fibrate therapy. If a severely depressed HDL-C level is detected, fibrate therapy should be withdrawn, and the HDL-C level monitored until it has returned to baseline, and fibrate therapy should not be re-initiated.

6 ADVERSE REACTIONS

6.1 Clinical Trials Experience

Because clinical trials are conducted under widely varying conditions, adverse reaction rates observed in the clinical trials of a drug cannot be directly compared to rates in the clinical trials of another drug and may not reflect the rates observed in clinical practice.

Adverse reactions reported by 2% or more of patients treated with fenofibrate (and greater than placebo) during the double-blind, placebo-controlled trials are listed in Table 1. Adverse reactions led to discontinuation of treatment in 5% of patients treated with fenofibrate and in 3% treated with placebo. Increases in liver function tests were the most frequent events, causing discontinuation of fenofibrate treatment in 1.6% of patients in double-blind trials.

Table 1. Adverse Reactions Reported by 2% or More of Patients Treated with Fenofibrate [Fenofibric acid is the active moiety of fenofibrate; Fenofibrate dosage equivalent to 105 mg fenofibric acid.] During the Double-Blind, Placebo-Controlled Trials
BODY SYSTEM Adverse Reactions | Fenofibrate (N=439) | Placebo (N=365)
BODY AS A WHOLE
Abdominal Pain | 4.6% | 4.4%
Back Pain | 3.4% | 2.5%
Headache | 3.2% | 2.7%
DIGESTIVE
Abnormal Liver Function Tests | 7.5% [Significantly different from Placebo.] | 1.4%
Nausea | 2.3% | 1.9%
Constipation | 2.1% | 1.4%
METABOLIC AND NUTRITIONAL DISORDERS
Increased ALT | 3.0% | 1.6%
Increased CPK | 3.0% | 1.4%
Increased AST | 3.4% | 0.5%
RESPIRATORY
Respiratory Disorder | 6.2% | 5.5%
Rhinitis | 2.3% | 1.1%

Urticaria was seen in 1.1 vs. 0%, and rash in 1.4 vs. 0.8% of fenofibrate and placebo patients respectively in controlled trials.

6.2 Postmarketing Experience

The following adverse reactions have been identified during post approval use of fenofibrate. Because these reactions are reported voluntarily from a population of uncertain size, it is not always possible to reliably estimate their frequency or establish a causal relationship to drug exposure: myalgia, rhabdomyolysis, pancreatitis, muscle spasm, acute renal failure, hepatitis, cirrhosis, anemia, headache, arthralgia, decreases in hemoglobin, decreases in hematocrit, white blood cell decreases, asthenia, and severely depressed HDL-cholesterol levels. Photosensitivity reactions have occurred days to months after initiation; in some of these cases, patients reported a prior photosensitivity reaction to ketoprofen.

7 DRUG INTERACTIONS

7.1 Coumarin Anticoagulants

Potentiation of coumarin-type anticoagulant effects has been observed with prolongation of the PT/INR.

Caution should be exercised when coumarin anticoagulants are given in conjunction with fenofibric acid tablets. The dosage of the anticoagulants should be reduced to maintain the prothrombin time/INR at the desired level to prevent bleeding complications. Frequent prothrombin time/INR determinations are advisable until it has been definitely determined that the prothrombin time/INR has stabilized [see Warnings and Precautions (5.6)].

7.2 Bile-Acid Binding Resins

Since bile-acid binding resins may bind other drugs given concurrently, patients should take fenofibric acid tablets at least 1 hour before or 4 to 6 hours after taking a bile-acid binding resin to avoid impeding its absorption.

7.3 Immunosuppressants

Immunosuppressant agents such as cyclosporine and tacrolimus can produce nephrotoxicity with decreases in creatinine clearance and rises in serum creatinine, and because renal excretion is the primary elimination route of fibrate drugs, including fenofibric acid tablets, there is a risk that an interaction will lead to deterioration of renal function. The benefits and risks of using fenofibric acid tablets with immunosuppressants and other potentially nephrotoxic agents should be carefully considered, and the lowest effective dose employed and renal function monitored.

7.4 Colchicine

Cases of myopathy, including rhabdomyolysis, have been reported with fenofibrates co-administered with colchicine, and caution should be exercised when prescribing fenofibrate with colchicine.

8 USE IN SPECIFIC POPULATIONS

8.1 Pregnancy

TERATOGENIC EFFECTS

Pregnancy Category C: Safety in pregnant women has not been established. There are no adequate and well controlled studies of fenofibrate in pregnant women. Fenofibric acid tablets should be used during pregnancy only if the potential benefit justifies the potential risk to the fetus.

In female rats given oral dietary doses of 15, 75, and 300 mg/kg/day of fenofibrate from 15 days prior to mating through weaning, maternal toxicity was observed at 0.3 times the maximum recommended human dose (MRHD), based on body surface area comparisons; mg per m^2.

In pregnant rats given oral dietary doses of 14, 127, and 361 mg/kg/day from gestation day 6–15 during the period of organogenesis, adverse developmental findings were not observed at 14 mg/kg/day (less than 1 times the MRHD, based on body surface area comparisons; mg per m^2). At higher multiples of human doses evidence of maternal toxicity was observed.

In pregnant rabbits given oral gavage doses of 15, 150, and 300 mg/kg/day from gestation day 6–18 during the period of organogenesis and allowed to deliver, aborted litters were observed at 150 mg/kg/day (10 times the MRHD based on body surface area comparisons; mg per m^2). No developmental findings were observed at 15 mg/kg/day (less than 1 times the MRHD, based on body surface area comparisons; mg per m^2).

In pregnant rats given oral dietary doses of 15, 75, and 300 mg/kg/day from gestation day 15 through lactation day 21 (weaning), maternal toxicity was observed at less than 1 times the MRHD, based on body surface area comparisons; mg per m^2 [see Nonclinical Toxicology (13.1)].

8.3 Nursing Mothers

Fenofibric acid tablets should not be used by nursing mothers. A decision should be made whether to discontinue nursing or to discontinue the drug, taking into account the importance of the drug to the mother [see Contraindications (4)].

8.4 Pediatric Use

Safety and effectiveness have not been established in pediatric patients.

8.5 Geriatric Use

Fenofibric acid tablets are substantially excreted by the kidney, and the risk of adverse reactions to this drug may be greater in patients with impaired renal function. Fenofibric acid exposure is not influenced by age. Since elderly patients have a higher incidence of renal impairment, dose selection for the elderly should be made on the basis of renal function [see Dosage and Administration (2.5) and Clinical Pharmacology (12.3)]. Elderly patients with normal renal function should require no dose modifications. Consider monitoring renal function in elderly patients taking fenofibric acid tablets.

8.6 Renal Impairment

The use of fenofibric acid tablets should be avoided in patients who have severe renal impairment [see Contraindications (4)]. Dose reduction is required in patients with mild-to-moderate renal impairment [see Dosage and Administration (2.4) and Clinical Pharmacology (12.3)]. Monitoring renal function in patients with renal impairment is recommended.

8.7 Hepatic Impairment

The use of fenofibric acid tablets has not been evaluated in patients with hepatic impairment [see Contraindications (4)].

10 OVERDOSAGE

There is no specific treatment for overdose with fenofibric acid tablets. General supportive care of the patient is indicated, including monitoring of vital signs and observation of clinical status, should an overdose occur. If indicated, elimination of unabsorbed drug should be achieved by emesis or gastric lavage; usual precautions should be observed to maintain the airway. Because fenofibric acid is highly bound to plasma proteins, hemodialysis should not be considered.

11 DESCRIPTION

Fenofibric acid is a lipid regulating agent available as tablets for oral administration. Each tablet contains 35 mg or 105 mg of fenofibric acid. The chemical name for fenofibric acid is 2-[4-(4-chlorobenzoyl)phenoxy]-2-methylpropanoic acid with the following structural formula:

Fenofibric acid is a white to almost white crystalline powder that is stable under ordinary conditions, and has a melting point of 179 – 183°C. Its empirical formula is C17H15ClO4 and molecular weight 318.75. Fenofibric acid is insoluble in water; its solubility increases with pH in buffered media.

Inactive Ingredients: Each tablet contains copovidone, crospovidone, magnesium stearate and microcrystalline cellulose.

12 CLINICAL PHARMACOLOGY

12.1 Mechanism of Action

The active moiety of fenofibric acid tablets is fenofibric acid. The pharmacological effects of fenofibric acid in both animals and humans have been extensively studied through oral administration of fenofibrate.

The lipid-modifying effects of fenofibric acid seen in clinical practice have been explained in vivo in transgenic mice and in vitro in human hepatocyte cultures by the activation of peroxisome proliferator activated receptor α (PPARα). Through this mechanism, fenofibric acid increases lipolysis and elimination of triglyceride-rich particles from plasma by activating lipoprotein lipase and reducing production of apoprotein C-III (an inhibitor of lipoprotein lipase activity). The resulting decrease in TG produces an alteration in the size and composition of LDL from small, dense particles to large buoyant particles. These larger particles have a greater affinity for cholesterol receptors and are catabolized rapidly. Activation of PPARα also induces an increase in the synthesis of apoproteins A-I, A-II and HDL-cholesterol.

Fenofibrate also reduces serum uric acid levels in hyperuricemic and normal individuals by increasing the urinary excretion of uric acid.

12.2 Pharmacodynamics

A variety of clinical studies have demonstrated that elevated levels of total-C, LDL-C, and apo B, an LDL membrane complex, are associated with human atherosclerosis. Similarly, decreased levels of HDL-C and its transport complex, apolipoprotein A (apo AI and apo AII) are associated with the development of atherosclerosis. Epidemiologic investigations have established that cardiovascular morbidity and mortality vary directly with the level of total-C, LDL-C, and TG, and inversely with the level of HDL-C. The independent effect of raising HDL-C or lowering triglycerides (TG) on the risk of cardiovascular morbidity and mortality has not been determined.

Fenofibric acid, the active metabolite of fenofibrate, produces reductions in total cholesterol, LDL cholesterol, apolipoprotein B, total triglycerides and triglyceride rich lipoprotein (VLDL) in treated patients. In addition, treatment with fenofibrate results in increases in high density lipoprotein (HDL) and apolipoproteins apo AI and apo AII.

12.3 Pharmacokinetics

Absorption

The absolute bioavailability of fenofibric acid tablets has not been determined as the compound is virtually insoluble in aqueous media suitable for injection. Following oral administration of fenofibric acid tablets in healthy volunteers, median peak plasma levels of fenofibric acid occur by approximately 2.5 hours after administration. Exposure after administration of 3 × 35 mg fenofibric acid tablets is comparable to 1 × 105 mg fenofibric acid tablets.

A food-effect study involving administration of fenofibric acid tablets to healthy volunteers under fasting conditions and with a high-fat meal indicated that the Cmax was decreased by approximately 35% while the AUC remained unchanged. This decrease in exposure is not considered clinically significant, and therefore fenofibric acid tablets can be taken without regards to meals.

The extent and rate of absorption of fenofibric acid after administration of 105 mg fenofibric acid tablets are equivalent to those after administration of 145 mg fenofibrate tablets (TriCor®) under fasted conditions.

Distribution

Upon multiple dosing of fenofibrate, fenofibric acid steady state is achieved within 9 days. Plasma concentrations of fenofibric acid at steady state are slightly more than double those following a single dose. Serum protein binding was approximately 99% in normal and hyperlipidemic subjects.

Metabolism

Fenofibric acid is primarily conjugated with glucuronic acid and then excreted in urine. A small amount of fenofibric acid is reduced at the carbonyl moiety to a benzhydrol metabolite which is, in turn, conjugated with glucuronic acid and excreted in urine.

In vitro and in vivo metabolism data indicate that fenofibric acid does not undergo oxidative metabolism (e.g. cytochrome P450) to a significant extent. The enzymes CYP1A2, CYP2A6, CYP2B6, CYP2C8, CYP2C9, CYP2C19, CYP2D6, CYP2E1, and CYP3A4 do not play a role in the metabolism of fenofibric acid.

Elimination

After absorption, fenofibric acid is eliminated with a half-life of approximately 20 hours, allowing once-daily dosing.

Specific Populations

Geriatrics: In five elderly volunteers 77 to 87 years of age, the oral clearance of fenofibric acid following a single oral dose of fenofibrate was 1.2 L/h, which compares to 1.1 L/h in young adults. This indicates that an equivalent dose of fenofibric acid tablets can be used in elderly subjects with normal renal function, without increasing accumulation of the drug or metabolites [see Use in Specific Populations (8.5) and Dosage and Administration (2.5)].

Pediatrics: The pharmacokinetics of fenofibric acid tablets has not been studied in pediatric populations.

Gender: No pharmacokinetic difference between males and females has been observed for fenofibrate.

Race: The influence of race on the pharmacokinetics of fenofibric acid has not been studied, however, fenofibric acid is not metabolized by enzymes known for exhibiting inter-ethnic variability.

Renal Impairment: The pharmacokinetics of fenofibric acid was examined in patients with mild, moderate, and severe renal impairment. Patients with severe renal impairment (Estimated glomerular filtration rate [eGFR]<30 mL/min/1.73m^2) showed a 2.7-fold increase in exposure for fenofibric acid and increased accumulation of fenofibric acid during chronic dosing compared to that of healthy subjects. Patients with mild-to-moderate (eGFR 30 – 59 mL/min/1.73m^2) renal impairment had similar exposure but an increase in the half-life for fenofibric acid compared to that of healthy subjects. Based on these findings, the use of fenofibric acid tablets should be avoided in patients who have severe renal impairment and dose reduction is required in patients with mild-to-moderate renal impairment.

Hepatic Impairment: No pharmacokinetic studies of fenofibric acid have been conducted in patients with hepatic impairment.

Drug-Drug Interactions: In vitro studies using human liver microsomes indicate that fenofibrate and fenofibric acid are not inhibitors of cytochrome (CYP) P450 isoforms CYP3A4, CYP2D6, CYP2E1, or CYP1A2. They are weak inhibitors of CYP2C8, CYP2C19 and CYP2A6, and mild-to-moderate inhibitors of CYP2C9 at therapeutic concentrations.

Table 2 describes the effects of co-administered drugs on fenofibric acid systemic exposure. Table 3 describes the effects of co-administered fenofibric acid on exposure to other drugs.

Table 2. Effects of Co-Administered Drugs on Fenofibric Acid Systemic Exposure from Fenofibric Acid Tablets or Fenofibrate Administration
Co-Administered Drug | Dosage Regimen of Co-Administered Drug | Dosage Regimen of Fenofibrate | Changes in Fenofibric Acid Exposure
Co-Administered Drug | Dosage Regimen of Co-Administered Drug | Dosage Regimen of Fenofibrate | AUC | Cmax
No dosing adjustment required for fenofibric acid tablets with the following co-administered drugs
Lipid-lowering agents
Atorvastatin | 20 mg once daily for 10 days | Fenofibrate 160 mg [TriCor® (fenofibrate) oral tablet] once daily for 10 days | ↓2% | ↓4%
Pravastatin | 40 mg as a single dose | Fenofibrate 3 × 67 mg [TriCor® (fenofibrate) oral micronized capsule] as a single dose | ↓1% | ↓2%
Fluvastatin | 40 mg as a single dose | Fenofibrate 160 mg as a single dose | ↓2% | ↓10%
Anti-diabetic agents
Glimepiride | 1 mg as a single dose | Fenofibrate 145 mg once daily for 10 days | ↑1% | ↓1%
Metformin | 850 mg three times daily for 10 days | Fenofibrate 54 mg three times daily for 10 days | ↓9% | ↓6%
Rosiglitazone | 8 mg once daily for 5 days | Fenofibrate 145 mg once daily for 14 days | ↑10% | ↑3%

Table 3. Effects of Fenofibric Acid Tablets or Fenofibrate Co-Administration on Systemic Exposure of Other Drugs
Dosage Regimen of Fenofibrate | Dosage Regimen of Co-Administered Drug | Change in Co-Administered Drug Exposure
Dosage Regimen of Fenofibrate | Dosage Regimen of Co-Administered Drug | Analyte | AUC | Cmax
No dosing adjustment required for these co-administered drugs with fenofibric acid tablets
Lipid-lowering agents
Fenofibrate 160 mg [TriCor® (fenofibrate) oral tablet] once daily for 10 days | Atorvastatin, 20 mg once daily for 10 days | Atorvastatin | ↓17% | 0%
Fenofibrate 3 × 67 mg [TriCor® (fenofibrate) oral micronized capsule] as a single dose | Pravastatin, 40 mg as a single dose | Pravastatin | ↑13% | ↑13%
 |  | 3α-Hydroxyl-iso-pravastatin | ↑26% | ↑29%
Fenofibrate 160 mg once daily for 10 days | Pravastatin, 40 mg once daily for 10 days | Pravastatin | ↑28% | ↑36%
 |  | 3α-Hydroxyl-iso-pravastatin | ↑39% | ↑55%
Fenofibrate 160 mg as a single dose | Fluvastatin, 40 mg as a single dose | (+)-3R, 5S-Fluvastatin | ↑15% | ↑16%
Anti-diabetic agents
Fenofibrate 145 mg once daily for 10 days | Glimepiride, 1 mg as a single dose | Glimepiride | ↑35% | ↑18%
Fenofibrate 54 mg three times daily for 10 days | Metformin, 850 mg three times daily for 10 days | Metformin | ↑3% | ↑6%
Fenofibrate 145 mg once daily for 14 days | Rosiglitazone, 8 mg once daily for 5 days | Rosiglitazone | ↑6% | ↓1%
Anti-viral agents
Fenofibric acid tablets 105 mg once daily for 10 days | Efavirenz, 600 mg as a single dose | Efavirenz | ↓8% | ↑1%

13 NONCLINICAL TOXICOLOGY

13.1 Carcinogenesis, Mutagenesis, Impairment of Fertility

Carcinogenesis

Two dietary carcinogenicity studies have been conducted in rats with fenofibrate. In the first 24-month study, Wistar rats were dosed with fenofibrate at 10, 45, and 200 mg/kg/day, approximately 0.3, 1, and 6 times the maximum recommended human (MRHD) dose, based on body surface area comparisons (mg/m^2). At a dose of 200 mg/kg/day (6 times the MRHD), the incidence of liver carcinomas was significantly increased in both sexes. A statistically significant increase in pancreatic carcinomas was observed in males at 1, and 6 times the MRHD; an increase in pancreatic adenomas and benign testicular interstitial cell tumors was observed at 6 times the MRHD in males. In a second 24-month rat carcinogenicity study in a different strain of rats (Sprague-Dawley), doses of 10 and 60 mg/kg/day (0.3 and 2 times the MRHD) produced significant increases in the incidence of pancreatic acinar adenomas in both sexes and increases in testicular interstitial cell tumors in males at 2 times the MRHD.

A 117-week carcinogenicity study was conducted in rats comparing three drugs: fenofibrate 10 and 60 mg/kg/day (0.3 and 2 times the MRHD of fenofibrate), clofibrate (400 mg/kg/day; 2 times the human dose), and gemfibrozil (250 mg/kg/day; 2 times the human dose, based on mg/meter^2 surface area). Fenofibrate increased pancreatic acinar adenomas in both sexes. Clofibrate increased hepatocellular carcinoma and pancreatic acinar adenomas in males and hepatic neoplastic nodules in females. Gemfibrozil increased hepatic neoplastic nodules in males and females, while all three drugs increased testicular interstitial cell tumors in males.

In a 21-month study in CF-1 mice, fenofibrate 10, 45, and 200 mg/kg/day (approximately 0.2, 1, and 3 times the human dose on the basis of mg/sq meter surface area) significantly increased the liver carcinomas in both sexes at doses that result in exposure to fenofibric acid that is 3 times the MRHD. In a second 18-month study at 10, 60, and 200 mg/kg/day, fenofibrate significantly increased the liver carcinomas in male mice and liver adenomas in female mice at 3 times the MRHD of fenofibrate.

Electron microscopy studies have demonstrated peroxisomal proliferation following fenofibrate administration to the rat. An adequate study to test for peroxisome proliferation in humans has not been done, but changes in peroxisome morphology and numbers have been observed in humans after treatment with other members of the fibrate class when liver biopsies were compared before and after treatment in the same individual.

Mutagenesis

Fenofibrate has been demonstrated to be devoid of mutagenic potential in the following tests: Ames, mouse lymphoma, chromosomal aberration and unscheduled DNA synthesis in primary rat hepatocytes.

Impairment of Fertility

In fertility studies, rats were given oral dietary doses of fenofibrate. Males received 61 days prior to mating and females 15 days prior to mating through weaning which resulted in no adverse effect on fertility at doses up to 300 mg/kg/day (approximately 10 times the MRHD of fenofibrate, based on mg/m^2 surface area comparisons).

14 CLINICAL STUDIES

14.1 Severe Hypertriglyceridemia

The effects of fenofibrate on serum triglycerides were studied in two randomized, double-blind, placebo-controlled clinical trials of 147 hypertriglyceridemic patients. Patients were treated for eight weeks under protocols that differed only in that one protocol entered patients with baseline triglyceride (TG) levels of 500 to 1500 mg/dL, and the other TG levels of 350 to 500 mg/dL.

In patients with hypertriglyceridemia and normal cholesterolemia with or without hyperchylomicronemia, treatment with fenofibrate at dosages equivalent to 105 mg of fenofibric acid tablets decreased primarily very low density lipoprotein (VLDL) triglycerides and VLDL cholesterol. Treatment of some with elevated triglycerides often results in an increase of low density lipoprotein (LDL) cholesterol (see Table 4).

Table 4. Effects of Fenofibrate in Patients with Severe Hypertriglyceridemia
Study 1 | Placebo |  |  |  | Fenofibrate
Baseline TG levels 350 to 499 mg/dL | N | Baseline (Mean) | Endpoint (Mean) | % Change (Mean) | N | Baseline (Mean) | Endpoint (Mean) | % Change (Mean)
Triglycerides | 28 | 449 | 450 | -0.5 | 27 | 432 | 223 | -46.2 [= p < 0.05 vs. Placebo]
VLDL Triglycerides | 19 | 367 | 350 | 2.7 | 19 | 350 | 178 | -44.1
Total Cholesterol | 28 | 255 | 261 | 2.8 | 27 | 252 | 227 | -9.1
HDL Cholesterol | 28 | 35 | 36 | 4 | 27 | 34 | 40 | 19.6
LDL Cholesterol | 28 | 120 | 129 | 12 | 27 | 128 | 137 | 14.5
VLDL Cholesterol | 27 | 99 | 99 | 5.8 | 27 | 92 | 46 | -44.7
Study 2 | Placebo |  |  |  | Fenofibrate
Baseline TG levels 500 to 1500 mg/dL | N | Baseline (Mean) | Endpoint (Mean) | % Change (Mean) | N | Baseline (Mean) | Endpoint (Mean) | % Change (Mean)
Triglycerides | 44 | 710 | 750 | 7.2 | 48 | 726 | 308 | -54.5
VLDL Triglycerides | 29 | 537 | 571 | 18.7 | 33 | 543 | 205 | -50.6
Total Cholesterol | 44 | 272 | 271 | 0.4 | 48 | 261 | 223 | -13.8
HDL Cholesterol | 44 | 27 | 28 | 5.0 | 48 | 30 | 36 | 22.9
LDL Cholesterol | 42 | 100 | 90 | -4.2 | 45 | 103 | 131 | 45.0
VLDL Cholesterol | 42 | 137 | 142 | 11.0 | 45 | 126 | 54 | -49.4

14.2 Primary Hypercholesterolemia (Heterozygous Familial and Nonfamilial) and Mixed Dyslipidemia

The effects of fenofibrate at doses equivalent to 105 mg of fenofibric acid tablets were assessed from four randomized, placebo-controlled, double-blind, parallel-group studies including patients with the following mean baseline lipid values: Total-C 306.9 mg/dL; LDL-C 213.8 mg/dL; HDL-C 52.3 mg/dL; and triglycerides 191.0 mg/dL. Fenofibrate therapy lowered LDL-C, Total-C, and the LDL-C/HDL-C ratio. Fenofibrate therapy also lowered triglycerides and raised HDL-C (see Table 5).

Table 5. Mean Percent Change in Lipid Parameters at End of Fenofibrate Treatment [Duration of study treatment was 3 to 6 months.]
Treatment Group | Total-C | LDL-C | HDL-C | TG
Pooled Cohort
Mean baseline lipid values (n=646) | 306.9 mg/dL | 213.8 mg/dL | 52.3 mg/dL | 191.0 mg/dL
All FEN (n=361) | -18.7% [p = < 0.05 vs. Placebo] | -20.6% | +11.0% | -28.9%
Placebo (n=285) | -0.4% | -2.2% | +0.7% | +7.7%
Baseline LDL-C >160 mg/dL and TG <150 mg/dL (Type IIa)
Mean baseline lipid values (n=334) | 307.7 mg/dL | 227.7 mg/dL | 58.1 mg/dL | 101.7 mg/dL
All FEN (n=193) | -22.4% | -31.4% | +9.8% | -23.5%
Placebo (n=141) | +0.2% | -2.2% | +2.6% | +11.7%
Baseline LDL-C >160 mg/dL and TG ≥150 mg/dL (Type IIb)
Mean baseline lipid values (n=242) | 312.8 mg/dL | 219.8 mg/dL | 46.7 mg/dL | 231.9 mg/dL
All FEN (n=126) | -16.8% | -20.1% | +14.6% | -35.9%
Placebo (n=116) | -3.0% | -6.6% | +2.3% | +0.9%

In a subset of the subjects, measurement of Apo B was conducted. Fenofibrate treatment significantly reduced Apo B from baseline to endpoint as compared with placebo (-25.1% vs. 2.4%, p < 0.0001, n=213 and 143 respectively).

The effect of fenofibric acid on cardiovascular morbidity and mortality has not been determined.

16 HOW SUPPLIED/STORAGE AND HANDLING

Fenofibric acid tablets 35 mg, are white, round tablets, debossed "AR 787" on one side and blank on the other side.

Bottles of 30 | NDC 69973-035-30

Fenofibric acid tablets 105 mg, are white, modified oval tablets, debossed "AR 788" on one side and blank on the other side.

Bottles of 30 | NDC 69973-105-30
Bottles of 90 | NDC 69973-105-90

STORAGE AND HANDLING

Store at USP controlled room temperature 20-25ºC (68-77ºF); excursions permitted to 15-30ºC (59-86ºF)

DISPENSE IN TIGHT, LIGHT-RESISTANT CONTAINER.

17 PATIENT COUNSELING INFORMATION

Patients should be advised:

- of the potential benefits and risks of fenofibric acid tablets.
- not to use fenofibric acid tablets if there is a known hypersensitivity to fenofibrate or fenofibric acid.
- that if they are taking coumarin anticoagulants, fenofibric acid tablets may increase their anticoagulant effect, and increased monitoring may be necessary.
- of medications that should not be taken in combination with fenofibric acid tablets.
- to continue to follow an appropriate lipid-modifying diet while taking fenofibric acid tablets.
- to take fenofibric acid tablets once daily, without regard to food, at the prescribed dose, swallowing each tablet whole.
- to inform their physician of all medications, supplements, and herbal preparations they are taking and any change to their medical condition. Patients should also be advised to inform their physicians prescribing a new medication that they are taking fenofibric acid tablets.
- to inform their physician of any muscle pain, tenderness, or weakness; onset of abdominal pain; or any other new symptoms.
- to return to their physician's office for routine monitoring.

TriCor® is a registered trademark of Abbott Laboratories.

Manufactured for: | Halton Laboratories
 | Princeton, NJ 08540

Revised 5/2018

———PRINCIPAL DISPLAY PANEL - 35 mg Tablet———

NDC 69973-035-30
Fenofibric Acid
Tablets
35 mg
Rx Only
30 Tablets Halton Laboratories

———PRINCIPAL DISPLAY PANEL - 105 mg Tablet———

NDC 69973-105-30
Fenofibric Acid
Tablets
105 mg
Rx Only
30 Tablets Halton Laboratories